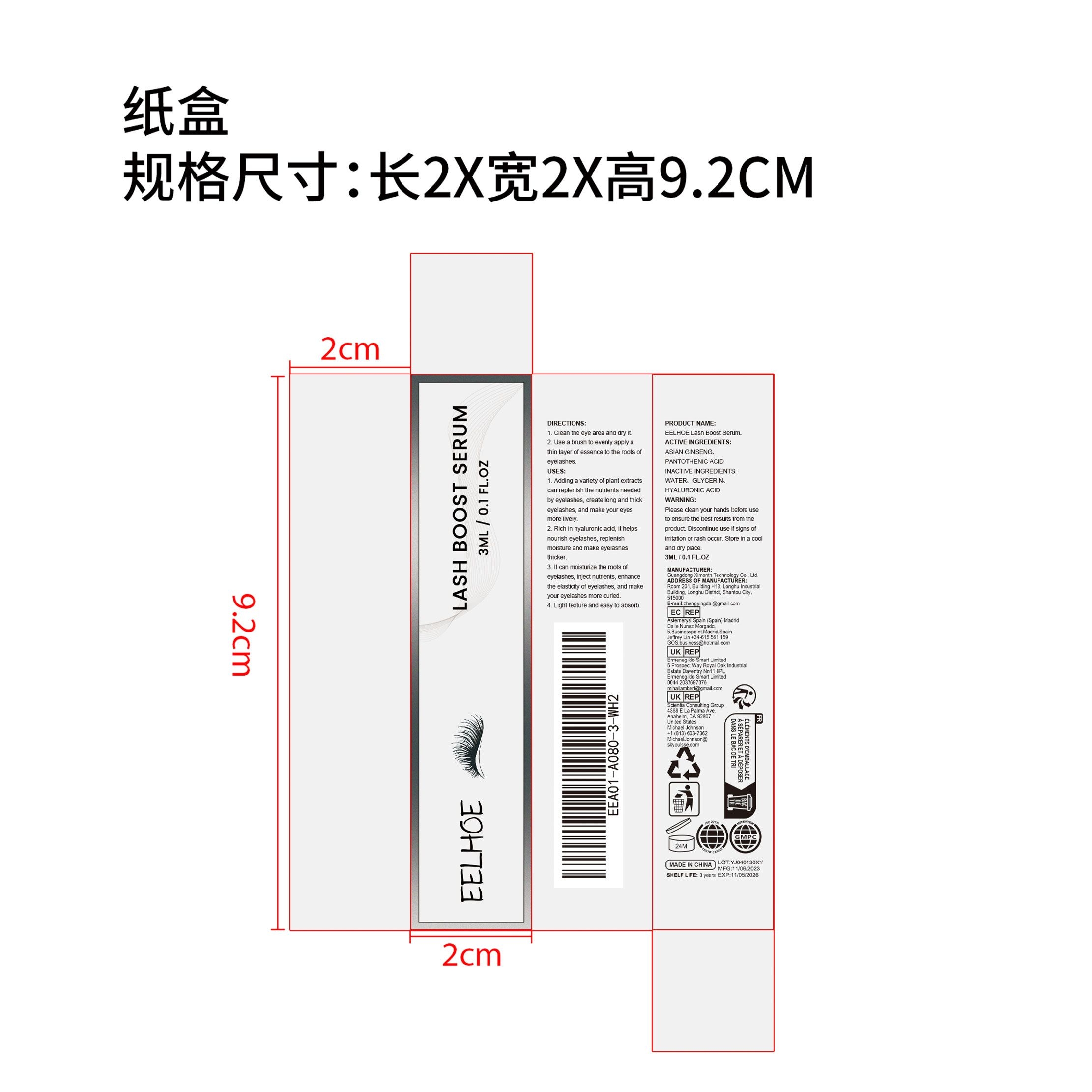 DRUG LABEL: EELHOE Lash Boost Serum
NDC: 84660-048 | Form: LIQUID
Manufacturer: Guangdong Ximonth Technology Co., Ltd.
Category: otc | Type: HUMAN OTC DRUG LABEL
Date: 20241026

ACTIVE INGREDIENTS: PANTOTHENIC ACID 0.6 mg/3 mg; ASIAN GINSENG 0.45 mg/3 mg
INACTIVE INGREDIENTS: HYALURONIC ACID 0.75 mg/3 mg; WATER 0.9 mg/3 mg; GLYCERIN 0.3 mg/3 mg

Active Ingredient(s)

ASIAN GINSENG、PANTOTHENIC ACID

Purpose

1. Adding a variety of plant extracts can replenish thenutrients needed by eyelashes, create long and thick eyelashes and make your eyes more lively
2. Rich in hyaluronic acid, it helps nourish eyelashes, replenish moisture and make eyelashes thicker.
3. It can moisturize the roots of eyelashes, inject nutrients, enhance the elasticity of eyelashes, and make your eyelashes more curled.
4. Light texture and easy to absorb.

Use

1. Clean the eye area and dry it.
2. Use a brush to evenly apply a thin layer of essence to the roots of eyelashes.

Warnings

Please keep out of reach of children.Do not swallow.Please clean your hands before use to ensure the best results from the product.Discontinue use if signs of irritation or rash occur.Store in a cool and dry place.

Do not use

Discontinue use if signs of irritation or rash occur.

Stop Use

Discontinue use if signs of irritation or rash occur.

STORAGE AND HANDLING

Store in a cool and dry place.

KEEP OUT OF REACH OF CHILDREN

Please keep out of reach of children. Do not swallow.

INACTIVE INGREDIENT

WATER、GLYCERIN、HYALURONIC ACID